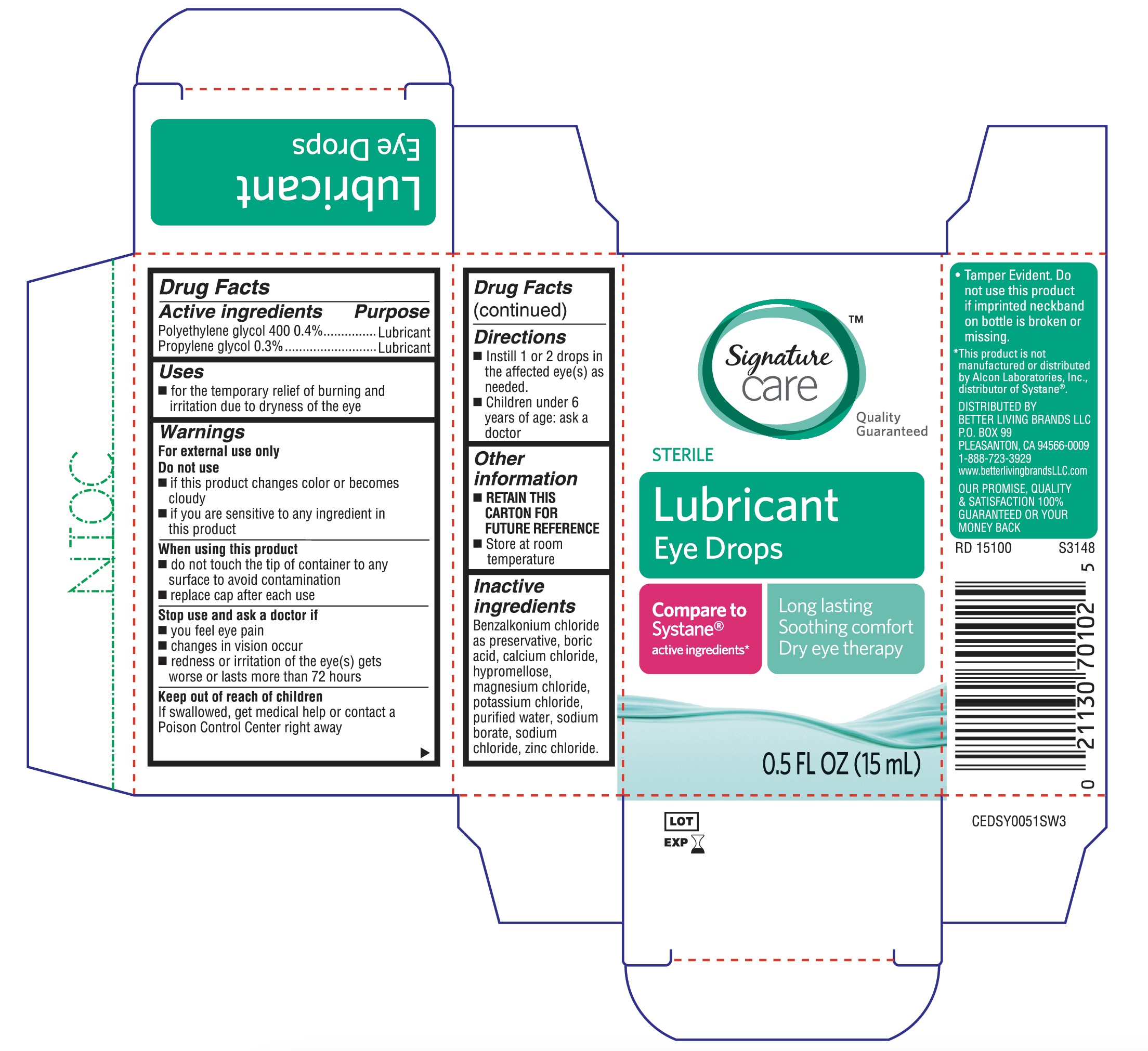 DRUG LABEL: Signature Care Lubricant Eye Drops Long Lasting
NDC: 21130-756 | Form: SOLUTION
Manufacturer: Better Living Brands, LLC
Category: otc | Type: HUMAN OTC DRUG LABEL
Date: 20231223

ACTIVE INGREDIENTS: POLYETHYLENE GLYCOL 400 0.4 g/100 mL; PROPYLENE GLYCOL 0.3 g/100 mL
INACTIVE INGREDIENTS: BENZALKONIUM CHLORIDE; BORIC ACID; CALCIUM CHLORIDE; MAGNESIUM CHLORIDE; POTASSIUM CHLORIDE; SODIUM BORATE; SODIUM CHLORIDE; ZINC CHLORIDE; WATER; HYPROMELLOSES

Signature Care Lubricant Eye Drops Long Lasting 15mL (PLD)

Active ingredients

polyethylene glycol 400 0.4%

propylene glycol 0.3%

Purpose

Lubricant

Lubricant

Uses

- for the temporary relief of burning and irritation due to dryness of the eye

Warnings

for external use only

Do not use

- if this product changes color or becomes cloudy
- if you are sensitive to any ingredient in this product

When using this product

- do not touch tip of container to any surface to avoid contamination
- replace cap after each use

Stop use and ask a doctor if

- you feel eye pain
- changes in vision occur
- redness or irritation of the eye(s), gets worse or lasts more than 72 hours

Keep out of reach of children

If swallowed, get medical help or contact a Poison Control Center right away

Directions

- Instill 1 or 2 drops in the affected eye(s) as needed.
- Children under 6 years of age: ask a doctor

Other information

- RETAIN THIS CARTON FOR FUTURE REFERENCE
- Store at room temperature

Inactive ingredients

Benzalkonium chloride as preservative, boric acid, calcium chloride, hypromellose, magnesium chloride, potassium chloride, purified water, sodium borate, sodium chloride, zinc chloride.